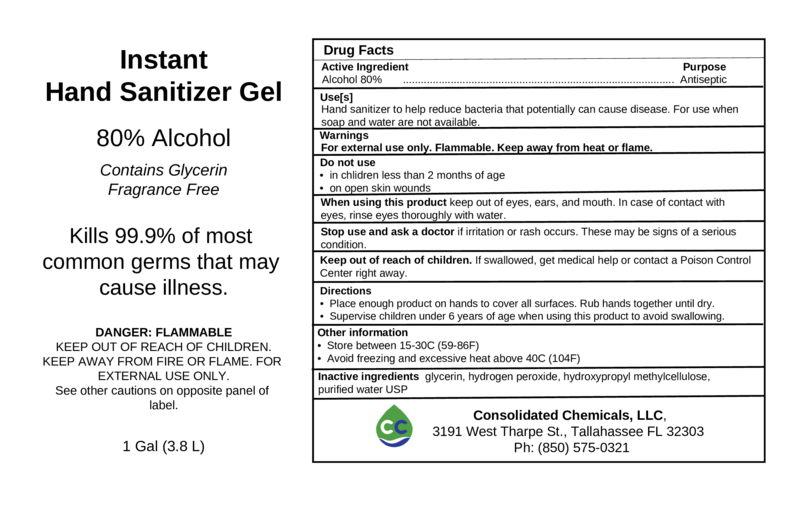 DRUG LABEL: Hand Sanitizer
NDC: 75632-210 | Form: GEL
Manufacturer: Consolidated Chemicals, LLC
Category: otc | Type: HUMAN OTC DRUG LABEL
Date: 20221229

ACTIVE INGREDIENTS: ALCOHOL 80 g/100 g
INACTIVE INGREDIENTS: GLYCERIN 2 g/100 g; HYDROGEN PEROXIDE 0.14 g/100 g; WATER; HYPROMELLOSE 2208 (100 MPA.S) 0.75 g/100 g

80% Alcohol Gel Sanitizer

Hand Sanitizer Alcohol Gel

This hand sanitizer is manufactured using the following ingredients in the preparation of the product (wt% in final product formulation) consistent with 21 CFR Part 310:

1. Alcohol (ethanol) (USP or Food Chemical Codex (FCC) grade) (80 wt%) in an aqueous solution denatured according to Alcohol and Tobacco Tax and Trade Bureau regulations in 27 CFR part 20.
2. Glycerol USP Grade (2 wt%).
3. Hydrogen peroxide (0.14 wt%).
4. Hydroxypropyl methylcellulose USP (0.75 wt%)
5. Distilled water

The firm does not add other active or inactive ingredients.

Active Ingredient(s)

Alcohol 80%. Purpose: Antiseptic

Purpose

Antiseptic, Hand Sanitizer

Use

Hand Sanitizer to help reduce bacteria that potentially can cause disease. For use when soap and water are not available.

Warnings

For external use only. Flammable. Keep away from heat or flame

Do not use

- in children less than 2 months of age
- on open skin wounds

When using this product keep out of eyes, ears, and mouth. In case of contact with eyes, rinse eyes thoroughly with water.
Stop use and ask a doctor if irritation or rash occurs. These may be signs of a serious condition.
Keep out of reach of children. If swallowed, get medical help or contact a Poison Control Center right away.

Stop use and ask a doctor if irritation or rash occurs. These may be signs of a serious condition.

Keep out of reach of children. If swallowed, get medical help or contact a Poison Control Center right away.

Directions

- Place enough product on hands to cover all surfaces. Rub hands together until dry.
- Supervise children under 6 years of age when using this product to avoid swallowing.

Other information

- Store between 15-30C (59-86F)
- Avoid freezing and excessive heat above 40C (104F)

Inactive ingredients

glycerin, hydrogen peroxide, hydroxypropyl methylcellulose, purified water USP

Package Label - Principal Display Panel

3784 mL NDC: 75632-210-40